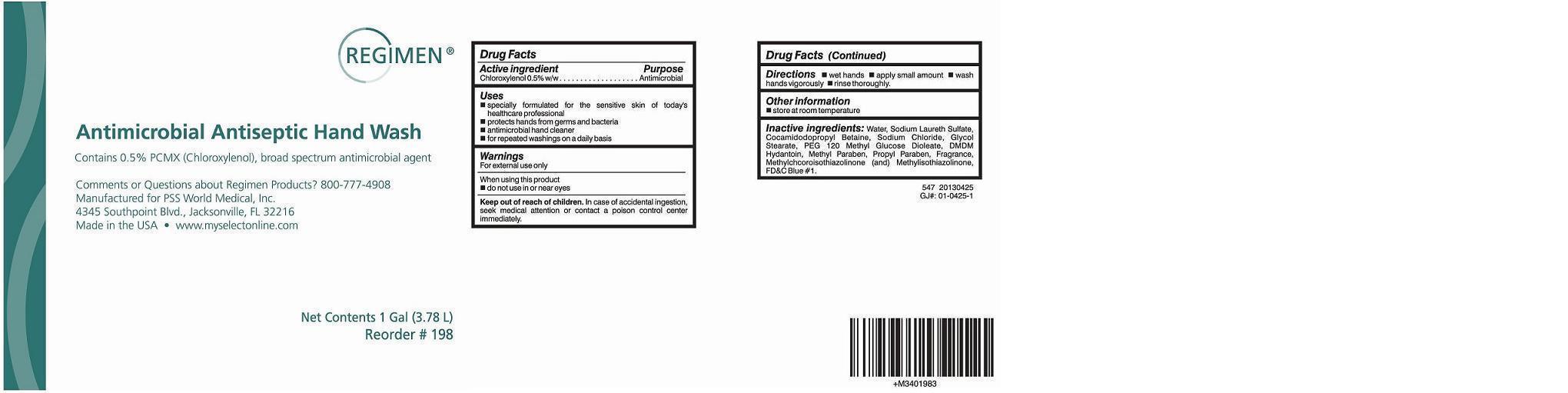 DRUG LABEL: REGIMEN ANTIMICROBIAL
NDC: 63843-547 | Form: SOAP
Manufacturer: HealthLink
Category: otc | Type: HUMAN OTC DRUG LABEL
Date: 20130924

ACTIVE INGREDIENTS: CHLOROXYLENOL 5 g/1000 mL
INACTIVE INGREDIENTS: WATER; GLYCOL STEARATE; SODIUM LAURETH SULFATE; METHYLPARABEN; PROPYLPARABEN; METHYLCHLOROISOTHIAZOLINONE; METHYLISOTHIAZOLINONE; COCAMIDOPROPYL BETAINE; DMDM HYDANTOIN; PEG-120 METHYL GLUCOSE DIOLEATE; SODIUM CHLORIDE

Active ingredient

Chloroxylenol 0.5% w/w

Purpose

Antimicrobial

Keep out of reach of children

In case of accidental ingestion, seek medical attention or contact a poison control center immediately.

Uses

- specially formulated for the sensitive skin of today's healthcare professional
- protects hands from germs and bacteria
- antimicrobial hand cleaner
- for repeated washings on a daily basis

Warnings

For external use only

When using this product

- do not use in or near eyes

Directions

 wet hands  apply small amount  wash hands vigorously  rinse thoroughly.

Other information

 store at room temperature

Inactive ingredients:

Water, Sodium Laureth Sulfate, Cocamidopropyl Betaine, Sodium Chloride, Glycol Stearate, PEG 120 Methyl Glucose Dioleate, DMDM Hydantoin, Fragrance, Methyl Paraben, Propyl Paraben, Methylchloroisothiazolinone (and) Methylisothiazolinone, FD&C Blue #1.